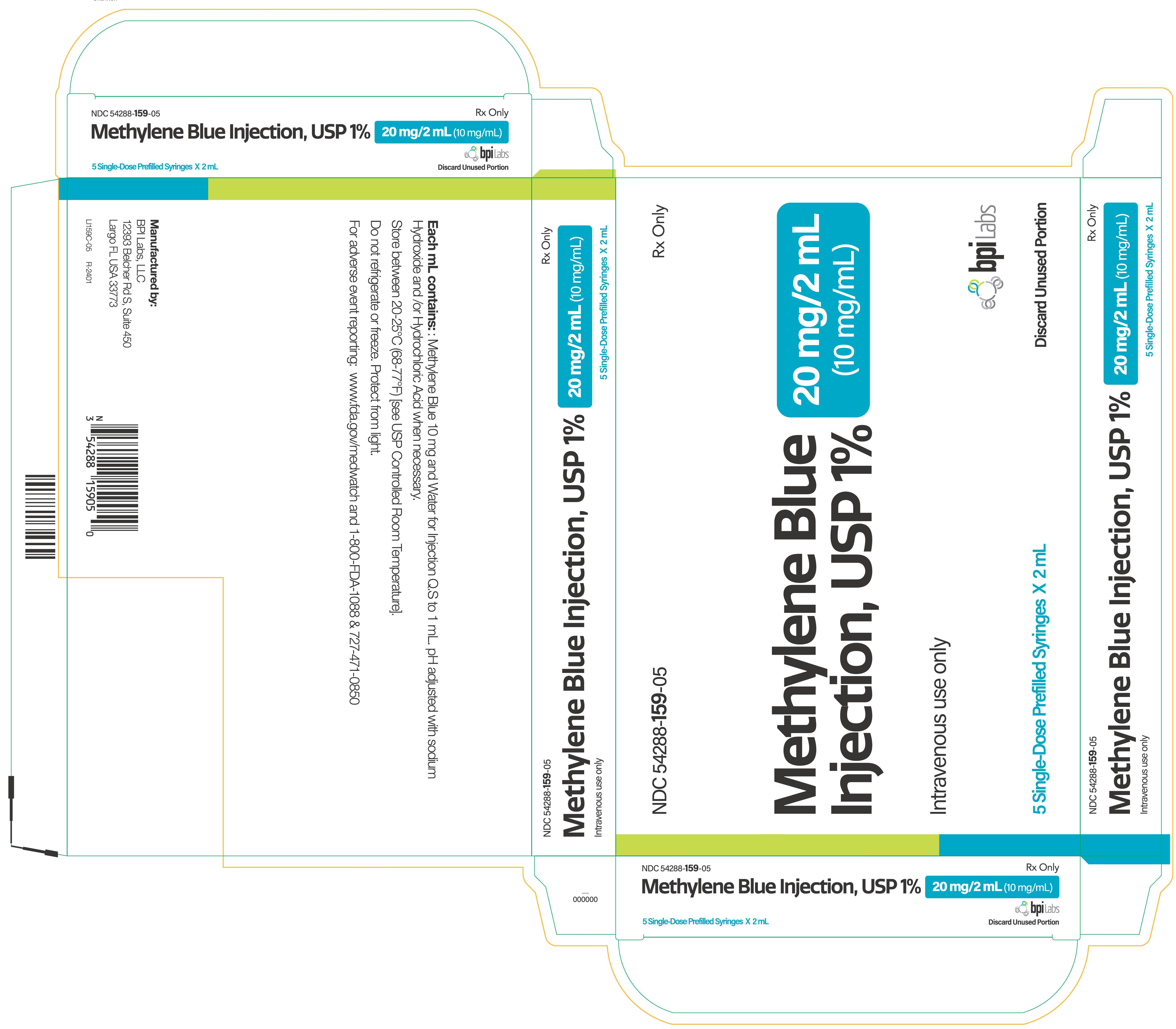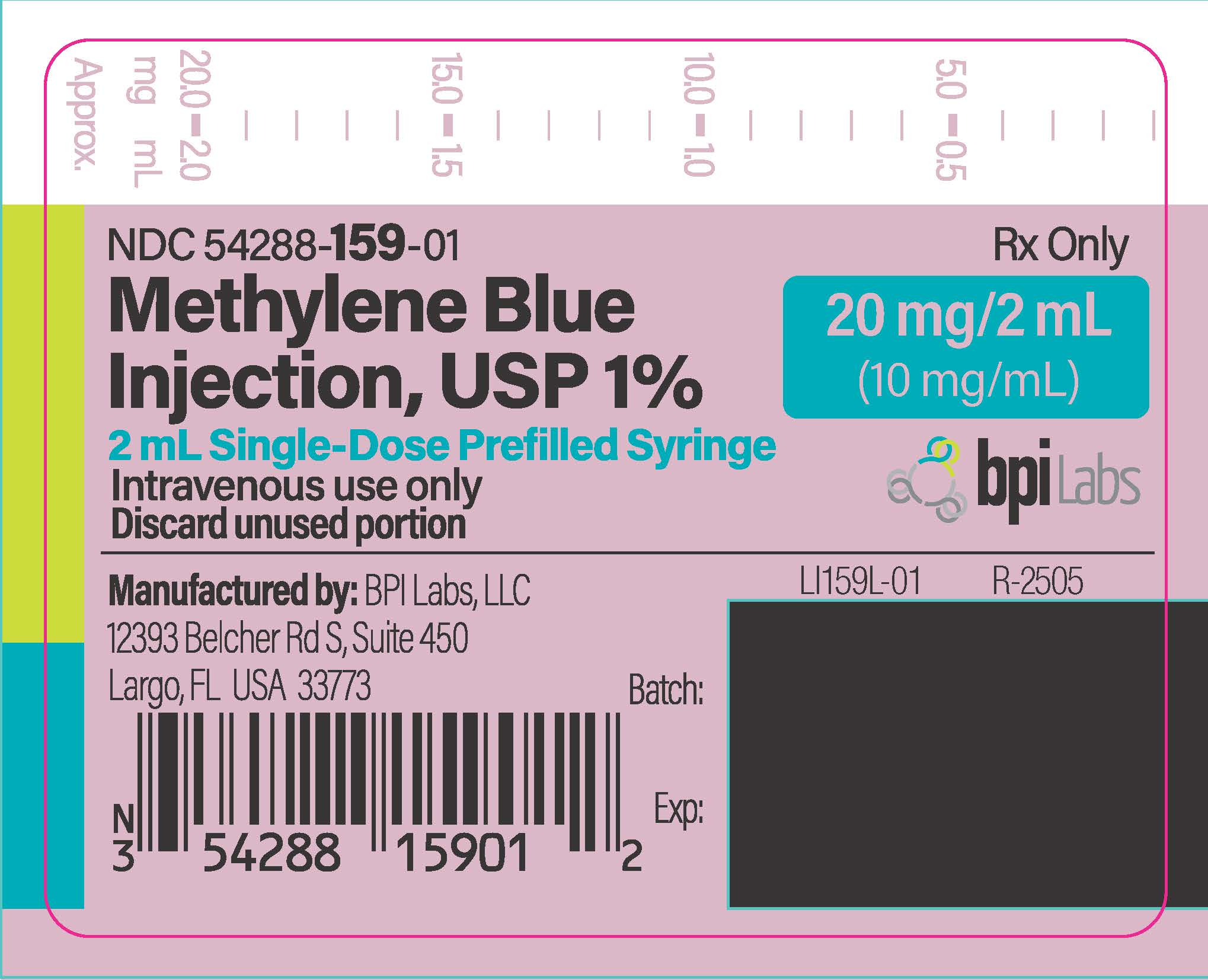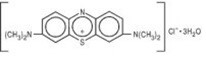 DRUG LABEL: Methylene Blue
NDC: 54288-159 | Form: INJECTION
Manufacturer: BPI LABS LLC
Category: prescription | Type: HUMAN PRESCRIPTION DRUG LABEL
Date: 20251226

ACTIVE INGREDIENTS: METHYLENE BLUE 10 mg/1 mL
INACTIVE INGREDIENTS: WATER; SODIUM HYDROXIDE; HYDROCHLORIC ACID

Methylene Blue Injection, USP 1%

(FOR SLOW INTRAVENOUS ADMINISTRATION)

Rx only

WARNING: SEROTONIN SYNDROME WITH CONCOMITANT USE OF SEROTONERGIC DRUGS

Methylene Blue Injection may cause serious or fatal serotonergic syndrome when used in combination with serotonergic drugs. Avoid concomitant use of Methylene Blue Injection with selective serotonin reuptake inhibitors (SSRIs), serotonin and norepinephrine reuptake inhibitors (SNRIs), and monoamine oxidase inhibitors (see WARNINGS and PRECAUTIONS, Drug Interactions).

DESCRIPTION :

Methylene Blue Injection is a sterile solution of Phenothiazin-5-ium, 3, 7-bis (dimethylamino)-, chloride, trihydrate. Each mL contains methylene blue, 10 mg in water for injection q.s. pH adjusted with sodium hydroxide and/or hydrochloric acid when necessary.

The structural formula is:

The molecular formula is:
C16H18ClN3S•3H2O MW = 373.90

CLINICAL PHARMACOLOGY :

Methylene blue will produce two opposite actions on hemoglobin. Low concentrations will convert methemoglobin to hemoglobin. High concentrations convert the ferrous iron of reduced hemoglobin to ferric iron which results in the formation of methemoglobin.

Methylene blue is metabolized in the body to leukomethylene blue which is excreted primarily in the urine. Some unchanged drug is also excreted in the urine. (1)

INDICATIONS AND USAGE :

Drug-induced methemoglobinemia

CONTRAINDICATIONS :

Methylene blue can cause fetal harm when administered to a pregnant woman. An association exists between the use of methylene blue in amniocentesis and atresia of the ileum and jejunum, ileal occlusions, and other adverse effects in the neonate. (2, 3)

Methylene blue is contraindicated in women who are or may become pregnant. If this drug is used during pregnancy, or if the patient becomes pregnant while taking this drug, the patient should be apprised of the potential hazard to the fetus.

Intraspinal and subcutaneous injections are contraindicated.

Methylene blue is contraindicated in patients with a known hypersensitivity to the drug.

WARNINGS :

Methylene blue should not be given by subcutaneous or intrathecal injection.

Methylene blue is a potent monoamine oxidase inhibitor:Methylene blue has been demonstrated to be a potent monoamine oxidase inhibitor (MAOI) and may cause potentially fatal serotonin toxicity (serotonin syndrome) when combined with serotonin reuptake inhibitors (SRIs). (4) (see DRUG INTERACTIONS.) Serotonin toxicity is characterized by development of neuromuscular hyperactivity (tremor, clonus, myoclonus, and hyperreflexia, and, in the advanced stage, pyramidal rigidity); autonomic hyperactivity (diaphoresis, fever, tachycardia, tachypnoea, and mydriasis); and altered mental status (agitation, excitement, and in the advanced stage, confusion). If methylene blue is judged to be indicated, SRIs must be ceased, prior to treatment/procedure/surgery.

PRECAUTIONS :

Drug Interactions:Methylene blue may interact with any drug that acts as a serotonin reuptake inhibitor (SRI) including, amongst others, selective serotonin reuptake inhibitors (SSRIs), serotonin and norepinephrine reuptake inhibitors (SNRIs), tricyclic antidepressants (TCAs), norepinephrine-dopamine reuptake inhibitors (NDRIs), triptans and ergot alkaloids; such combinations may have the consequence of potentially fatal serotonin toxicity (serotonin syndrome). Methylene blue should not be co- administered with any drug that acts as an SRI.

Pregnancy: Pregnancy Category X:Epidemiologic evidence exists that methylene blue is a teratogen. An association exists between the use of methylene blue in amniocentesis and atresia of the ileum and jejunum, ileal occlusions, and other adverse effects in the neonate. (2,3) Methylene blue injection should not be administered to pregnant women during amniocentesis due to the risk of teratogenicity and other newborn adverse effects (see CONTRAINDICATIONS).

Glucose-6-Phosphate Dehydrogenase Deficiency (G6PD Deficiency):Methylene blue should be avoided in patients with G6PD deficiency due to the risk of paradoxical methemoglobinemia and hemolysis. (5,6)

Renal Failure:Methylene blue should be used with caution in patients with severe renal impairment (see CLINICAL PHARMACOLOGY).

Methylene blue must be injected intravenously very slowly over a period of several minutes to prevent local high concentration of the compound from producing additional methemoglobin. Do not exceed recommended dosage.

Large intravenous doses of methylene blue produce nausea, abdominal and precordial pain, dizziness, headache, profuse sweating, mental confusion, and the formation of methemoglobin.

DOSAGE AND ADMINISTRATION :

0.1 to 0.2 mL per kg body weight (0.045 to 0.09 mL per pound body weight). Inject methylene blue intravenously very slowly over a period of several minutes.

Methylene blue must be injected intravenously very slowly over a period of several minutes to prevent local high concentration of the compound from producing additional methemoglobin. Do not exceed recommended dosage. Parenteral drug products should be inspected visually for particulate matter and discoloration, whenever solution and container permit.

HOW SUPPLIED :

Methylene Blue Injection, USP 1% is supplied as follows:

NDC 54288-159-05

Five 2 mL Single-Dose Prefilled Syringes packed in a carton

To report SUSPECTED ADVERSE REACTIONS, contact BPI Labs LLC at 727-471-0850 or FDA at 1-800-FDA-1088 or www.fda.gov/medwatch.

STORAGE :

Store at 20° to 25°C (68° to 77°F) [see USP Controlled Room Temperature].

REFERENCES :

1. DiSanto AR, Wagner JG. Pharmacokinetics of highly ionized drugs II: methylene blue – absorption, metabolism, and excretion in man and dog after oral administration. J Pharm Sci. 1972; 61:1086- 1090.
2. Cragan JD. Teratogen update: methylene blue. Teratology. 1999; 60:42-48.
3. Kidd SA, Lancaster PA, Anderson JC, Boogert A, Fisher CC, Robertson R, et al. Fetal death after exposure to methylene blue dye during mid-trimester amniocentesis in twin pregnancy. Prenat Diagn. 1996; 16:39-47.
4. Ramsay RR, Dunford C, Gillman PK. Methylene blue and serotonin toxicity: inhibition of monoamine oxidase A (MAOA) confirms a theoretical prediction. Br J Pharmacol. 2007; 152:946-51.
5. Beutler E. G6PD Deficiency. Blood. 1994; 84:3613-3636.
6. Youngster I, Arcavi L, Schechmaster R, Akayzen Y, Popliski H, Shimonov J, Beig S, Berkovitch M. Medications and glucose-6-phosphate dehydrogenase deficiency: an evidence-based review. Drug Saf. 2010; 33:713-726.

Manufactured by:

BPI Labs, LLC

12393 Belcher Road S, Suite 450

Largo, FL 33773

LI50I

R-2401